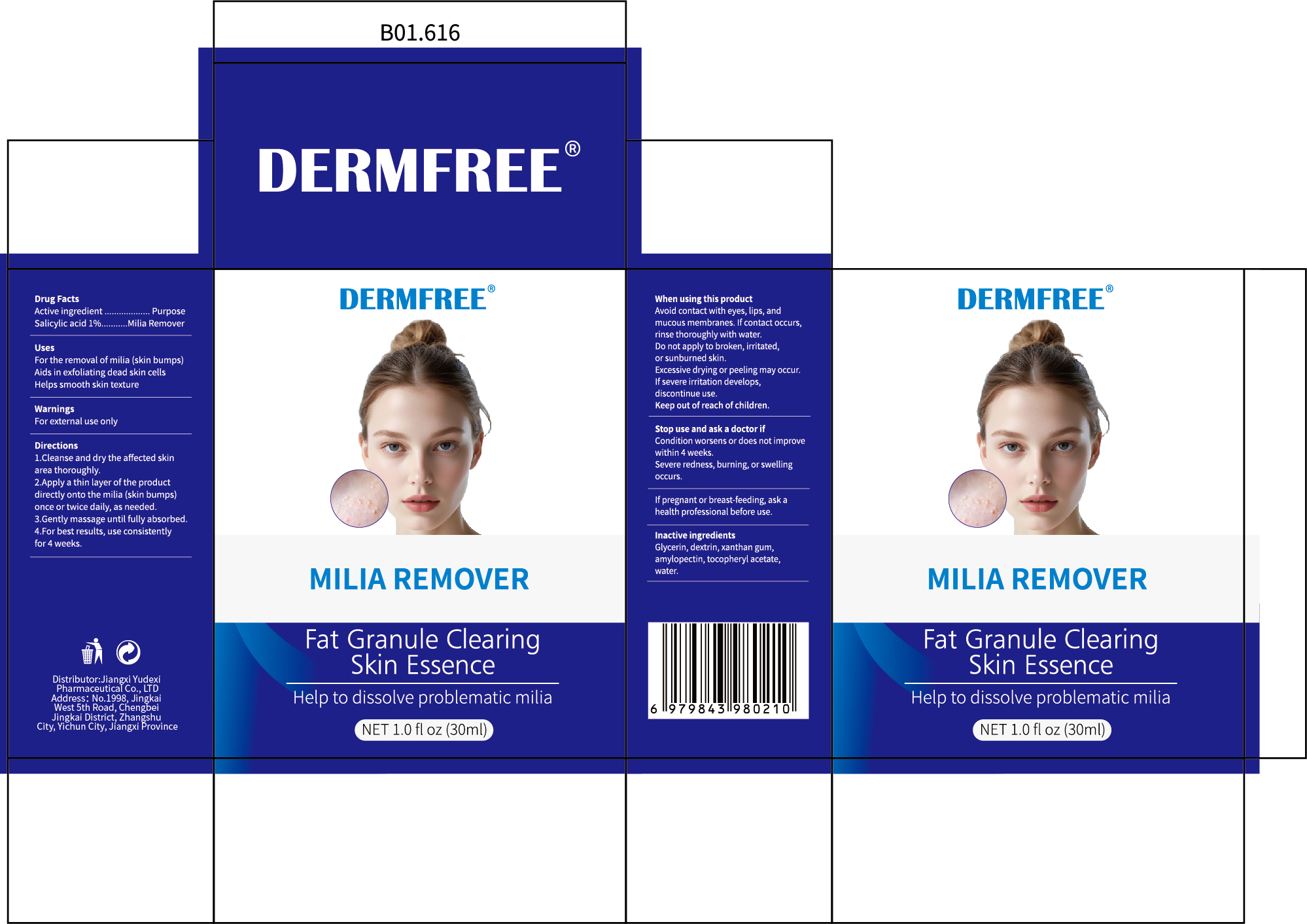 DRUG LABEL: DERMFREE  MILIA REMOVER
NDC: 85248-125 | Form: LIQUID
Manufacturer: Jiangxi Yudexi Pharmaceutical Co., LTD
Category: otc | Type: HUMAN OTC DRUG LABEL
Date: 20260208

ACTIVE INGREDIENTS: SALICYLIC ACID 1 g/100 mL
INACTIVE INGREDIENTS: DEXTRIN, CORN; .ALPHA.-TOCOPHEROL ACETATE; GLYCERIN; WATER; AMYLOPECTIN, CORN

85248-125

Active Ingredient

Salicylic acid 1%

Purpose

Milia Remover

Use

For the removal of milia (skin bumps)Aids in exfoliating dead skin cells Helps smooth skin texture

Warnings

For external use only

Do not use

Do not apply to broken, irritated,or sunburned skin.
Excessive drying or peeling may occur.If severe irritation develops

When Using

When using this product Avoid contact with eyes, lips, and mucous membranes. If contact occurs,rinse thoroughly with water.Do not apply to broken, irritated,or sunburned skin.Excessive drying or peeling may occur.If severe irritation develops,discontinue use.Keep out of reach of children.

Stop Use

Stop use and ask a doctor if Condition worsens or does not improve within 4 weeks.Severe redness, burning, or swelling occurs

Ask Doctor

ask a doctor if Condition worsens or does not improve within 4 weeks.Severe redness, burning, or swelling occurs.If pregnant or breast-feeding, ask a health professional before use.

Keep Oot Of Reach Of Children

Keep out of reach of children.

Directions

L.Cleanse and dry the affected skin
area thoroughly.2.Apply a thin layer of the product directly onto the milia (skin bumps) once or twice daily, as needed.3.Gently massage until fully absorbed.4.For best results, use consistently for 4 weeks.

Inactive ingredients

Glycerin, dextrin, xanthan gum,amylopectin, tocopheryl acetate,water.